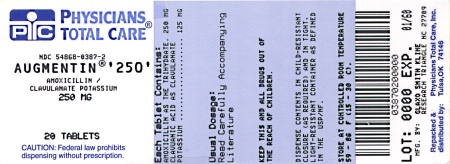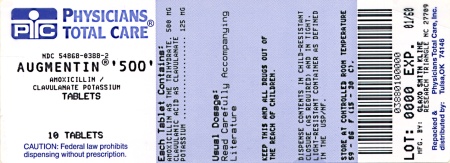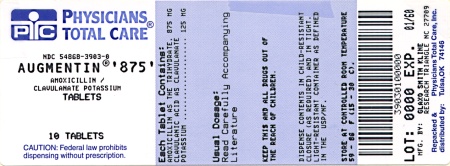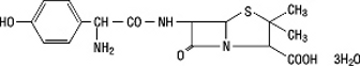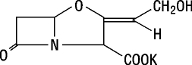 DRUG LABEL: Augmentin
NDC: 54868-0387 | Form: TABLET, FILM COATED
Manufacturer: Physicians Total Care, Inc.
Category: prescription | Type: HUMAN PRESCRIPTION DRUG LABEL
Date: 20101122

ACTIVE INGREDIENTS: AMOXICILLIN 250 mg/1 1; CLAVULANATE POTASSIUM 125 mg/1 1
INACTIVE INGREDIENTS: SILICON DIOXIDE; HYPROMELLOSES; MAGNESIUM STEARATE; CELLULOSE, MICROCRYSTALLINE; POLYETHYLENE GLYCOL; SODIUM STARCH GLYCOLATE TYPE A POTATO; TITANIUM DIOXIDE

To reduce the development of drug-resistant bacteria and maintain the effectiveness of AUGMENTIN (amoxicillin/clavulanate potassium) and other antibacterial drugs, AUGMENTIN should be used only to treat or prevent infections that are proven or strongly suspected to be caused by bacteria.

DESCRIPTION

AUGMENTIN is an oral antibacterial combination consisting of the semisynthetic antibiotic amoxicillin and the β-lactamase inhibitor, clavulanate potassium (the potassium salt of clavulanic acid). Amoxicillin is an analog of ampicillin, derived from the basic penicillin nucleus, 6-aminopenicillanic acid. The amoxicillin molecular formula is C16H19N3O5S•3H2O, and the molecular weight is 419.46. Chemically, amoxicillin is (2S,5R,6R)-6-[(R)-(-)-2-Amino-2-(p-hydroxyphenyl)acetamido]-3,3-dimethyl-7-oxo-4-thia-1-azabicyclo[3.2.0]heptane-2-carboxylic acid trihydrate and may be represented structurally as:

Clavulanic acid is produced by the fermentation of Streptomyces clavuligerus. It is a β-lactam structurally related to the penicillins and possesses the ability to inactivate a wide variety of β-lactamases by blocking the active sites of these enzymes. Clavulanic acid is particularly active against the clinically important plasmid-mediated β-lactamases frequently responsible for transferred drug resistance to penicillins and cephalosporins. The clavulanate potassium molecular formula is C8H8KNO5, and the molecular weight is 237.25. Chemically, clavulanate potassium is potassium (Z)-(2R, 5R)-3-(2-hydroxyethylidene)-7-oxo-4-oxa-1-azabicyclo[3.2.0]-heptane-2-carboxylate, and may be represented structurally as:

Inactive Ingredients

Colloidal silicon dioxide, hypromellose, magnesium stearate, microcrystalline cellulose, polyethylene glycol, sodium starch glycolate, and titanium dioxide.

Each tablet of AUGMENTIN contains 0.63 mEq potassium.

CLINICAL PHARMACOLOGY

Amoxicillin and clavulanate potassium are well absorbed from the gastrointestinal tract after oral administration of AUGMENTIN. Dosing in the fasted or fed state has minimal effect on the pharmacokinetics of amoxicillin. While AUGMENTIN can be given without regard to meals, absorption of clavulanate potassium when taken with food is greater relative to the fasted state. In 1 study, the relative bioavailability of clavulanate was reduced when AUGMENTIN was dosed at 30 and 150 minutes after the start of a high-fat breakfast. The safety and efficacy of AUGMENTIN have been established in clinical trials where AUGMENTIN was taken without regard to meals.

Meana amoxicillin and clavulanate potassium pharmacokinetic parameters are shown in the table below:

Doseb and regimen | AUC0-24 (mcg•hr/mL) | Cmax (mcg/mL)
amoxicillin/; clavulanate potassium | amoxicillin (±S.D.) | clavulanate potassium (±S.D.) | amoxicillin (±S.D.) | clavulanate potassium (±S.D.)
250/125 mg q8h | 26.7 ± 4.56 | 12.6 ± 3.25 | 3.3 ± 1.12 | 1.5 ± 0.70
500/125 mg q12h | 33.4 ± 6.76 | 8.6 ± 1.95 | 6.5 ± 1.41 | 1.8 ± 0.61
500/125 mg q8h | 53.4 ± 8.87 | 15.7 ± 3.86 | 7.2 ± 2.26 | 2.4 ± 0.83
875/125 mg q12h | 53.5 ± 12.31 | 10.2 ± 3.04 | 11.6 ± 2.78 | 2.2 ± 0.99

a Mean values of 14 normal volunteers (n = 15 for clavulanate potassium in the low-dose regimens). Peak concentrations occurred approximately 1.5 hours after the dose.

b Administered at the start of a light meal.

Amoxicillin serum concentrations achieved with AUGMENTIN are similar to those produced by the oral administration of equivalent doses of amoxicillin alone. The half-life of amoxicillin after the oral administration of AUGMENTIN is 1.3 hours and that of clavulanic acid is 1.0 hour.

Approximately 50% to 70% of the amoxicillin and approximately 25% to 40% of the clavulanic acid are excreted unchanged in urine during the first 6 hours after administration of a single 250-mg or 500-mg tablet of AUGMENTIN.

Concurrent administration of probenecid delays amoxicillin excretion but does not delay renal excretion of clavulanic acid.

Neither component in AUGMENTIN is highly protein-bound; clavulanic acid has been found to be approximately 25% bound to human serum and amoxicillin approximately 18% bound.

Amoxicillin diffuses readily into most body tissues and fluids with the exception of the brain and spinal fluid. The results of experiments involving the administration of clavulanic acid to animals suggest that this compound, like amoxicillin, is well distributed in body tissues.

Microbiology

Amoxicillin is a semisynthetic antibiotic with a broad spectrum of bactericidal activity against many gram-positive and gram-negative microorganisms. Amoxicillin is, however, susceptible to degradation by β-lactamases, and therefore, the spectrum of activity does not include organisms which produce these enzymes. Clavulanic acid is a β-lactam, structurally related to the penicillins, which possesses the ability to inactivate a wide range of β-lactamase enzymes commonly found in microorganisms resistant to penicillins and cephalosporins. In particular, it has good activity against the clinically important plasmid-mediated β-lactamases frequently responsible for transferred drug resistance.

The formulation of amoxicillin and clavulanic acid in AUGMENTIN protects amoxicillin from degradation by β-lactamase enzymes and effectively extends the antibiotic spectrum of amoxicillin to include many bacteria normally resistant to amoxicillin and other β-lactam antibiotics. Thus, AUGMENTIN possesses the properties of a broad-spectrum antibiotic and a β-lactamase inhibitor.

Amoxicillin/clavulanic acid has been shown to be active against most strains of the following microorganisms, both in vitro and in clinical infections as described in INDICATIONS AND USAGE.

Gram-Positive Aerobes

Staphylococcus aureus (β-lactamase and non−β-lactamase−producing)c

c Staphylococci which are resistant to methicillin/oxacillin must be considered resistant to amoxicillin/clavulanic acid.

Gram-Negative Aerobes

Enterobacter species (Although most strains of Enterobacter species are resistant in vitro, clinical efficacy has been demonstrated with AUGMENTIN in urinary tract infections caused by these organisms.)

Escherichia coli (β-lactamase and non−β-lactamase−producing)

Haemophilus influenzae (β-lactamase and non−β-lactamase−producing)

Klebsiella species (All known strains are β-lactamase−producing.)

Moraxella catarrhalis (β-lactamase and non−β-lactamase−producing)

The following in vitro data are available, but their clinical significance is unknown.

Amoxicillin/clavulanic acid exhibits in vitro minimal inhibitory concentrations (MICs) of 2 mcg/mL or less against most (≥ 90%) strains of Streptococcus pneumoniae d; MICs of 0.06 mcg/mL or less against most (≥ 90%) strains of Neisseria gonorrhoeae ; MICs of 4 mcg/mL or less against most (≥ 90%) strains of staphylococci and anaerobic bacteria; and MICs of 8 mcg/mL or less against most (≥ 90%) strains of other listed organisms. However, with the exception of organisms shown to respond to amoxicillin alone, the safety and effectiveness of amoxicillin/clavulanic acid in treating clinical infections due to these microorganisms have not been established in adequate and well-controlled clinical trials.

d Because amoxicillin has greater in vitro activity against S. pneumoniae than does ampicillin or penicillin, the majority of S. pneumoniae strains with intermediate susceptibility to ampicillin or penicillin are fully susceptible to amoxicillin.

Gram-Positive Aerobes

Enterococcus faecalise

Staphylococcus epidermidis (β-lactamase and non−β-lactamase−producing)

Staphylococcus saprophyticus (β-lactamase and non−β-lactamase−producing)

Streptococcus pneumoniaee f

Streptococcus pyogenese f

viridans group Streptococcuse f

Gram-Negative Aerobes

Eikenella corrodens (β-lactamase and non−β-lactamase−producing)

Neisseria gonorrhoeaee (β-lactamase and non–β-lactamase–producing)

Proteus mirabilise (β-lactamase and non–β-lactamase–producing)

Anaerobic Bacteria

Bacteroides species, including Bacteroides fragilis (β-lactamase and non–β-lactamase–producing)

Fusobacterium species (β-lactamase and non–β-lactamase–producing)

Peptostreptococcus speciesf

e Adequate and well-controlled clinical trials have established the effectiveness of amoxicillin alone in treating certain clinical infections due to these organisms.

f These are non–β-lactamase−producing organisms, and therefore, are susceptible to amoxicillin alone.

Susceptibility Testing Dilution Techniques

Quantitative methods are used to determine antimicrobial MICs. These MICs provide estimates of the susceptibility of bacteria to antimicrobial compounds. The MICs should be determined using a standardized procedure. Standardized procedures are based on a dilution method^1 (broth or agar) or equivalent with standardized inoculum concentrations and standardized concentrations of amoxicillin/clavulanate potassium powder.

The recommended dilution pattern utilizes a constant amoxicillin/clavulanate potassium ratio of 2 to 1 in all tubes with varying amounts of amoxicillin. MICs are expressed in terms of the amoxicillin concentration in the presence of clavulanic acid at a constant 2 parts amoxicillin to 1 part clavulanic acid. The MIC values should be interpreted according to the following criteria: RECOMMENDED RANGES FOR AMOXICILLIN/CLAVULANIC ACID SUSCEPTIBILITY TESTING

For Gram-Negative Enteric Aerobes:

MIC (mcg/mL) | Interpretation
≤ 8/4 | Susceptible (S)
16/8 | Intermediate (I)
≥ 32/16 | Resistant (R)

For Staphylococcusg and Haemophilus species:

MIC (mcg/mL) | Interpretation
≤ 4/2 | Susceptible (S)
≥ 8/4 | Resistant (R)

g Staphylococci which are susceptible to amoxicillin/clavulanic acid but resistant to methicillin/oxacillin must be considered as resistant.

For S. pneumoniae from non-meningitis sources:

Isolates should be tested using amoxicillin/clavulanic acid and the following criteria should be used:

MIC (mcg/mL) | Interpretation
≤ 2/1 | Susceptible (S)
4/2 | Intermediate (I)
≥ 8/4 | Resistant (R)

NOTE: These interpretive criteria are based on the recommended doses for respiratory tract infections.

A report of “Susceptible” indicates that the pathogen is likely to be inhibited if the antimicrobial compound in the blood reaches the concentration usually achievable. A report of “Intermediate” indicates that the result should be considered equivocal, and, if the microorganism is not fully susceptible to alternative, clinically feasible drugs, the test should be repeated. This category implies possible clinical applicability in body sites where the drug is physiologically concentrated or in situations where high dosage of drug can be used. This category also provides a buffer zone, which prevents small uncontrolled technical factors from causing major discrepancies in interpretation. A report of “Resistant” indicates that the pathogen is not likely to be inhibited if the antimicrobial compound in the blood reaches the concentrations usually achievable; other therapy should be selected.

Standardized susceptibility test procedures require the use of laboratory control microorganisms to control the technical aspects of the laboratory procedures. Standard amoxicillin/clavulanate potassium powder should provide the following MIC values:

Microorganism | MIC Range (mcg/mL)h
Escherichia coli ATCC 25922 | 2 to 8
Escherichia coli ATCC 35218 | 4 to 16
Enterococcus faecalis ATCC 29212 | 0.25 to 1.0
Haemophilus influenzae ATCC 49247 | 2 to 16
Staphylococcus aureus ATCC 29213 | 0.12 to 0.5
Streptococcus pneumoniae ATCC 49619 | 0.03 to 0.12

h Expressed as concentration of amoxicillin in the presence of clavulanic acid at a constant 2 parts amoxicillin to 1 part clavulanic acid.

Diffusion Techniques

Quantitative methods that require measurement of zone diameters also provide reproducible estimates of the susceptibility of bacteria to antimicrobial compounds. One such standardized procedure^2 requires the use of standardized inoculum concentrations. This procedure uses paper disks impregnated with 30 mcg of amoxicillin/clavulanate potassium (20 mcg amoxicillin plus 10 mcg clavulanate potassium) to test the susceptibility of microorganisms to amoxicillin/clavulanic acid.

Reports from the laboratory providing results of the standard single-disk susceptibility test with a 30-mcg amoxicillin/clavulanate acid (20 mcg amoxicillin plus 10 mcg clavulanate potassium) disk should be interpreted according to the following criteria: RECOMMENDED RANGES FOR AMOXICILLIN/CLAVULANIC ACID SUSCEPTIBILITY TESTING

For Staphylococcusi species and H. influenzaej:

Zone Diameter (mm) | Interpretation
≥ 20 | Susceptible (S)
≤ 19 | Resistant (R)

For Other Organisms Except S. pneumoniaek and N. gonorrhoeael:

Zone Diameter (mm) | Interpretation
≥ 18 | Susceptible (S)
14 to 17 | Intermediate (I)
≤ 13 | Resistant (R)

i Staphylococci which are resistant to methicillin/oxacillin must be considered as resistant to amoxicillin/clavulanic acid.

j A broth microdilution method should be used for testing H. influenzae. Beta-lactamase−negative, ampicillin-resistant strains must be considered resistant to amoxicillin/clavulanic acid.

k Susceptibility of S. pneumoniae should be determined using a 1-mcg oxacillin disk. Isolates with oxacillin zone sizes of ≥2 0 mm are susceptible to amoxicillin/clavulanic acid. An amoxicillin/clavulanic acid MIC should be determined on isolates of S. pneumoniae with oxacillin zone sizes of ≤1 9 mm.

l A broth microdilution method should be used for testing N. gonorrhoeae and interpreted according to penicillin breakpoints.

Interpretation should be as stated above for results using dilution techniques. Interpretation involves correlation of the diameter obtained in the disk test with the MIC for amoxicillin/clavulanic acid.

As with standardized dilution techniques, diffusion methods require the use of laboratory control microorganisms that are used to control the technical aspects of the laboratory procedures. For the diffusion technique, the 30-mcg amoxicillin/clavulanate potassium (20-mcg amoxicillin plus 10-mcg clavulanate potassium) disk should provide the following zone diameters in these laboratory quality control strains:

Microorganism | Zone Diameter (mm)
Escherichia coli ATCC 25922 | 19 to 25
Escherichia coli ATCC 35218 | 18 to 22
Staphylococcus aureus ATCC 25923 | 28 to 36

INDICATIONS AND USAGE

AUGMENTIN is indicated in the treatment of infections caused by susceptible strains of the designated organisms in the conditions listed below:

Lower Respiratory Tract Infections

− caused by β-lactamase−producing strains of H. influenzae and M. catarrhalis.

Otitis Media

− caused by β-lactamase−producing strains of H. influenzae and M. catarrhalis.

Sinusitis

− caused by β-lactamase−producing strains of H. influenzae and M. catarrhalis.

Skin and Skin Structure Infections

− caused by β-lactamase−producing strains of S. aureus, E. coli, and Klebsiella spp.

Urinary Tract Infections

− caused by β-lactamase−producing strains of E. coli, Klebsiella spp., and Enterobacter spp.

While AUGMENTIN is indicated only for the conditions listed above, infections caused by ampicillin-susceptible organisms are also amenable to treatment with AUGMENTIN due to its amoxicillin content; therefore, mixed infections caused by ampicillin-susceptible organisms and β-lactamase−producing organisms susceptible to AUGMENTIN should not require the addition of another antibiotic. Because amoxicillin has greater in vitro activity against S. pneumoniae than does ampicillin or penicillin, the majority of S. pneumoniae strains with intermediate susceptibility to ampicillin or penicillin are fully susceptible to amoxicillin and AUGMENTIN. (See Microbiology.)

To reduce the development of drug-resistant bacteria and maintain the effectiveness of AUGMENTIN and other antibacterial drugs, AUGMENTIN should be used only to treat or prevent infections that are proven or strongly suspected to be caused by susceptible bacteria. When culture and susceptibility information are available, they should be considered in selecting or modifying antibacterial therapy. In the absence of such data, local epidemiology and susceptibility patterns may contribute to the empiric selection of therapy.

Bacteriological studies, to determine the causative organisms and their susceptibility to AUGMENTIN, should be performed together with any indicated surgical procedures.

CONTRAINDICATIONS

AUGMENTIN is contraindicated in patients with a history of allergic reactions to any penicillin. It is also contraindicated in patients with a previous history of cholestatic jaundice/hepatic dysfunction associated with AUGMENTIN.

WARNINGS

SERIOUS AND OCCASIONALLY FATAL HYPERSENSITIVITY (ANAPHYLACTIC) REACTIONS HAVE BEEN REPORTED IN PATIENTS ON PENICILLIN THERAPY. THESE REACTIONS ARE MORE LIKELY TO OCCUR IN INDIVIDUALS WITH A HISTORY OF PENICILLIN HYPERSENSITIVITY AND/OR A HISTORY OF SENSITIVITY TO MULTIPLE ALLERGENS. THERE HAVE BEEN REPORTS OF INDIVIDUALS WITH A HISTORY OF PENICILLIN HYPERSENSITIVITY WHO HAVE EXPERIENCED SEVERE REACTIONS WHEN TREATED WITH CEPHALOSPORINS. BEFORE INITIATING THERAPY WITH AUGMENTIN, CAREFUL INQUIRY SHOULD BE MADE CONCERNING PREVIOUS HYPERSENSITIVITY REACTIONS TO PENICILLINS, CEPHALOSPORINS, OR OTHER ALLERGENS. IF AN ALLERGIC REACTION OCCURS, AUGMENTIN SHOULD BE DISCONTINUED AND THE APPROPRIATE THERAPY INSTITUTED. SERIOUS ANAPHYLACTIC REACTIONS REQUIRE IMMEDIATE EMERGENCY TREATMENT WITH EPINEPHRINE. OXYGEN, INTRAVENOUS STEROIDS, AND AIRWAY MANAGEMENT, INCLUDING INTUBATION, SHOULD ALSO BE ADMINISTERED AS INDICATED.

Clostridium difficile associated diarrhea (CDAD) has been reported with use of nearly all antibacterial agents, including AUGMENTIN, and may range in severity from mild diarrhea to fatal colitis. Treatment with antibacterial agents alters the normal flora of the colon leading to overgrowth of C. difficile.

C. difficile produces toxins A and B which contribute to the development of CDAD. Hypertoxin producing strains of C. difficile. cause increased morbidity and mortality, as these infections can be refractory to antimicrobial therapy and may require colectomy. CDAD must be considered in all patients who present with diarrhea following antibiotic use. Careful medical history is necessary since CDAD has been reported to occur over two months after the administration of antibacterial agents.

If CDAD is suspected or confirmed, ongoing antibiotic use not directed against C. difficile. may need to be discontinued. Appropriate fluid and electrolyte management, protein supplementation, antibiotic treatment of C. difficile, and surgical evaluation should be instituted as clinically indicated.

AUGMENTIN should be used with caution in patients with evidence of hepatic dysfunction. Hepatic toxicity associated with the use of AUGMENTIN is usually reversible. On rare occasions, deaths have been reported (less than 1 death reported per estimated 4 million prescriptions worldwide). These have generally been cases associated with serious underlying diseases or concomitant medications. (See CONTRAINDICATIONS and ADVERSE REACTIONS: Liver.)

PRECAUTIONS

General

While AUGMENTIN possesses the characteristic low toxicity of the penicillin group of antibiotics, periodic assessment of organ system functions, including renal, hepatic, and hematopoietic function, is advisable during prolonged therapy.

A high percentage of patients with mononucleosis who receive ampicillin develop an erythematous skin rash. Thus, ampicillin-class antibiotics should not be administered to patients with mononucleosis.

The possibility of superinfections with mycotic or bacterial pathogens should be kept in mind during therapy. If superinfections occur (usually involving Pseudomonas or Candida), the drug should be discontinued and/or appropriate therapy instituted.

Prescribing AUGMENTIN in the absence of a proven or strongly suspected bacterial infection or a prophylactic indication is unlikely to provide benefit to the patient and increases the risk of the development of drug-resistant bacteria.

Drug Interactions

Probenecid decreases the renal tubular secretion of amoxicillin. Concurrent use with AUGMENTIN may result in increased and prolonged blood levels of amoxicillin. Coadministration of probenecid cannot be recommended.

Abnormal prolongation of prothrombin time (increased international normalized ratio [INR]) has been reported rarely in patients receiving amoxicillin and oral anticoagulants. Appropriate monitoring should be undertaken when anticoagulants are prescribed concurrently. Adjustments in the dose of oral anticoagulants may be necessary to maintain the desired level of anticoagulation.

The concurrent administration of allopurinol and ampicillin increases substantially the incidence of rashes in patients receiving both drugs as compared to patients receiving ampicillin alone. It is not known whether this potentiation of ampicillin rashes is due to allopurinol or the hyperuricemia present in these patients. There are no data with AUGMENTIN and allopurinol administered concurrently.

In common with other broad-spectrum antibiotics, AUGMENTIN may reduce the efficacy of oral contraceptives.

Drug/Laboratory Test Interactions

Oral administration of AUGMENTIN will result in high urine concentrations of amoxicillin. High urine concentrations of ampicillin may result in false-positive reactions when testing for the presence of glucose in urine using CLINITEST®, Benedict’s Solution, or Fehling’s Solution. Since this effect may also occur with amoxicillin and therefore AUGMENTIN, it is recommended that glucose tests based on enzymatic glucose oxidase reactions (such as CLINISTIX®) be used.

Following administration of ampicillin to pregnant women, a transient decrease in plasma concentration of total conjugated estriol, estriol-glucuronide, conjugated estrone and estradiol has been noted. This effect may also occur with amoxicillin and therefore AUGMENTIN.

Information for Patients

Patients should be counseled that antibacterial drugs including AUGMENTIN, should only be used to treat bacterial infections. They do not treat viral infections (e.g., the common cold). When AUGMENTIN is prescribed to treat a bacterial infection, patients should be told that although it is common to feel better early in the course of therapy, the medication should be taken exactly as directed. Skipping doses or not completing the full course of therapy may: (1) decrease the effectiveness of the immediate treatment, and (2) increase the likelihood that bacteria will develop resistance and will not be treatable by AUGMENTIN or other antibacterial drugs in the future.

Diarrhea is a common problem caused by antibiotics which usually ends when the antibiotic is discontinued. Sometimes after starting treatment with antibiotics, patients can develop watery and bloody stools (with or without stomach cramps and fever) even as late as two or more months after having taken the last dose of the antibiotic. If this occurs, patients should contact their physician as soon as possible.

Carcinogenesis, Mutagenesis, Impairment of Fertility

Long-term studies in animals have not been performed to evaluate carcinogenic potential.

Mutagenesis

The mutagenic potential of AUGMENTIN was investigated in vitro with an Ames test, a human lymphocyte cytogenetic assay, a yeast test and a mouse lymphoma forward mutation assay, and in vivo with mouse micronucleus tests and a dominant lethal test. All were negative apart from the in vitro mouse lymphoma assay where weak activity was found at very high, cytotoxic concentrations.

Impairment of Fertility

AUGMENTIN at oral doses of up to 1,200 mg/kg/day (5.7 times the maximum human dose, 1,480 mg/m^2/day, based on body surface area) was found to have no effect on fertility and reproductive performance in rats, dosed with a 2:1 ratio formulation of amoxicillin:clavulanate.

Pregnancy Teratogenic Effects

Pregnancy (Category B). Reproduction studies performed in pregnant rats and mice given AUGMENTIN at oral dosages up to 1,200 mg/kg/day, equivalent to 7,200 and 4,080 mg/m^2/day, respectively (4.9 and 2.8 times the maximum human oral dose based on body surface area), revealed no evidence of harm to the fetus due to AUGMENTIN. There are, however, no adequate and well-controlled studies in pregnant women. Because animal reproduction studies are not always predictive of human response, this drug should be used during pregnancy only if clearly needed.

Labor and Delivery

Oral ampicillin-class antibiotics are generally poorly absorbed during labor. Studies in guinea pigs have shown that intravenous administration of ampicillin decreased the uterine tone, frequency of contractions, height of contractions, and duration of contractions; however, it is not known whether the use of AUGMENTIN in humans during labor or delivery has immediate or delayed adverse effects on the fetus, prolongs the duration of labor, or increases the likelihood that forceps delivery or other obstetrical intervention or resuscitation of the newborn will be necessary. In a single study in women with premature rupture of fetal membranes, it was reported that prophylactic treatment with AUGMENTIN may be associated with an increased risk of necrotizing enterocolitis in neonates.

Nursing Mothers

Ampicillin-class antibiotics are excreted in the milk; therefore, caution should be exercised when AUGMENTIN is administered to a nursing woman.

Pediatric Use

Pediatric patients weighing 40 kg or more should be dosed according to the adult recommendations (see DOSAGE AND ADMINISTRATION: Pediatric Patients). Safety and effectiveness of AUGMENTIN Tablets in pediatric patients weighing less than 40 kg have not been established. (See prescribing information for AUGMENTIN Powder for Oral Suspension and Chewable Tablets.)

Geriatric Use

An analysis of clinical studies of AUGMENTIN was conducted to determine whether subjects aged 65 and over respond differently from younger subjects. Of the 3,119 patients in this analysis, 68% were <65 years old, 32% were >65 years old and 14% were >75 years old. This analysis and other reported clinical experience have not identified differences in responses between the elderly and younger patients, but a greater sensitivity of some older individuals cannot be ruled out.

This drug is known to be substantially excreted by the kidney, and the risk of toxic reactions to this drug may be greater in patients with impaired renal function. Because elderly patients are more likely to have decreased renal function, care should be taken in dose selection, and it may be useful to monitor renal function.

ADVERSE REACTIONS

AUGMENTIN is generally well tolerated. The majority of side effects observed in clinical trials were of a mild and transient nature and less than 3% of patients discontinued therapy because of drug-related side effects. The most frequently reported adverse effects were diarrhea/loose stools (9%), nausea (3%), skin rashes and urticaria (3%), vomiting (1%) and vaginitis (1%). The overall incidence of side effects, and in particular diarrhea, increased with the higher recommended dose. Other less frequently reported reactions include: Abdominal discomfort, flatulence, and headache.

The following adverse reactions have been reported for ampicillin-class antibiotics:

Gastrointestinal

Diarrhea, nausea, vomiting, indigestion, gastritis, stomatitis, glossitis, black “hairy” tongue, mucocutaneous candidiasis, enterocolitis, and hemorrhagic/pseudomembranous colitis. Onset of pseudomembranous colitis symptoms may occur during or after antibiotic treatment. (See WARNINGS.)

Hypersensitivity Reactions

Skin rashes, pruritus, urticaria, angioedema, serum sickness−like reactions (urticaria or skin rash accompanied by arthritis, arthralgia, myalgia, and frequently fever), erythema multiforme (rarely Stevens-Johnson syndrome), acute generalized exanthematous pustulosis, hypersensitivity vasculitis, and an occasional case of exfoliative dermatitis (including toxic epidermal necrolysis) have been reported. These reactions may be controlled with antihistamines and, if necessary, systemic corticosteroids. Whenever such reactions occur, the drug should be discontinued, unless the opinion of the physician dictates otherwise. Serious and occasional fatal hypersensitivity (anaphylactic) reactions can occur with oral penicillin. (See WARNINGS.)

Liver

A moderate rise in AST (SGOT) and/or ALT (SGPT) has been noted in patients treated with ampicillin-class antibiotics but the significance of these findings is unknown. Hepatic dysfunction, including hepatitis and cholestatic jaundice, [see CONTRAINDICATIONS], increases in serum transaminases (AST and/or ALT), serum bilirubin, and/or alkaline phosphatase, has been infrequently reported with AUGMENTIN. It has been reported more commonly in the elderly, in males, or in patients on prolonged treatment. The histologic findings on liver biopsy have consisted of predominantly cholestatic, hepatocellular, or mixed cholestatic-hepatocellular changes. The onset of signs/symptoms of hepatic dysfunction may occur during or several weeks after therapy has been discontinued. The hepatic dysfunction, which may be severe, is usually reversible. On rare occasions, deaths have been reported (less than 1 death reported per estimated 4 million prescriptions worldwide). These have generally been cases associated with serious underlying diseases or concomitant medications.

Renal

Interstitial nephritis and hematuria have been reported rarely. Crystalluria has also been reported (see OVERDOSAGE).

Hemic and Lymphatic Systems

Anemia, including hemolytic anemia, thrombocytopenia, thrombocytopenic purpura, eosinophilia, leukopenia, and agranulocytosis have been reported during therapy with penicillins. These reactions are usually reversible on discontinuation of therapy and are believed to be hypersensitivity phenomena. A slight thrombocytosis was noted in less than 1% of the patients treated with AUGMENTIN. There have been reports of increased prothrombin time in patients receiving AUGMENTIN and anticoagulant therapy concomitantly.

Central Nervous System

Agitation, anxiety, behavioral changes, confusion, convulsions, dizziness, insomnia, and reversible hyperactivity have been reported rarely.

Miscellaneous

Tooth discoloration (brown, yellow, or gray staining) has been rarely reported. Most reports occurred in pediatric patients. Discoloration was reduced or eliminated with brushing or dental cleaning in most cases.

OVERDOSAGE

Following overdosage, patients have experienced primarily gastrointestinal symptoms including stomach and abdominal pain, vomiting, and diarrhea. Rash, hyperactivity, or drowsiness have also been observed in a small number of patients.

In the case of overdosage, discontinue AUGMENTIN, treat symptomatically, and institute supportive measures as required. If the overdosage is very recent and there is no contraindication, an attempt at emesis or other means of removal of drug from the stomach may be performed. A prospective study of 51 pediatric patients at a poison center suggested that overdosages of less than 250 mg/kg of amoxicillin are not associated with significant clinical symptoms and do not require gastric emptying.^3

Interstitial nephritis resulting in oliguric renal failure has been reported in a small number of patients after overdosage with amoxicillin.

Crystalluria, in some cases leading to renal failure, has also been reported after amoxicillin overdosage in adult and pediatric patients. In case of overdosage, adequate fluid intake and diuresis should be maintained to reduce the risk of amoxicillin crystalluria.

Renal impairment appears to be reversible with cessation of drug administration. High blood levels may occur more readily in patients with impaired renal function because of decreased renal clearance of both amoxicillin and clavulanate. Both amoxicillin and clavulanate are removed from the circulation by hemodialysis. (See DOSAGE AND ADMINISTRATION for recommended dosing for patients with impaired renal function.)

DOSAGE AND ADMINISTRATION

Since both the 250-mg and 500-mg tablets of AUGMENTIN contain the same amount of clavulanic acid (125 mg, as the potassium salt), two 250-mg tablets of AUGMENTIN are not equivalent to one 500-mg tablet of AUGMENTIN; therefore, two 250-mg tablets of AUGMENTIN should not be substituted for one 500-mg tablet of AUGMENTIN.

Dosage Adults

The usual adult dose is one 500-mg tablet of AUGMENTIN every 12 hours or one 250-mg tablet of AUGMENTIN every 8 hours. For more severe infections and infections of the respiratory tract, the dose should be one 875-mg tablet of AUGMENTIN every 12 hours or one 500-mg tablet of AUGMENTIN every 8 hours.

Patients with impaired renal function do not generally require a reduction in dose unless the impairment is severe. Severely impaired patients with a glomerular filtration rate of <30 mL/min. should not receive the 875-mg tablet. Patients with a glomerular filtration rate of 10 to 30 mL/min. should receive 500 mg or 250 mg every 12 hours, depending on the severity of the infection. Patients with a less than 10 mL/min. glomerular filtration rate should receive 500 mg or 250 mg every 24 hours, depending on severity of the infection.

Hemodialysis patients should receive 500 mg or 250 mg every 24 hours, depending on severity of the infection. They should receive an additional dose both during and at the end of dialysis.

Hepatically impaired patients should be dosed with caution and hepatic function monitored at regular intervals. (See WARNINGS.)

Pediatric Patients

Pediatric patients weighing 40 kg or more should be dosed according to the adult recommendations.

Due to the different amoxicillin to clavulanic acid ratios in the 250-mg tablet of AUGMENTIN (250/125) versus the 250-mg chewable tablet of AUGMENTIN (250/62.5), the 250-mg tablet of AUGMENTIN should not be used until the pediatric patient weighs at least 40 kg or more.

Administration

AUGMENTIN may be taken without regard to meals; however, absorption of clavulanate potassium is enhanced when AUGMENTIN is administered at the start of a meal. To minimize the potential for gastrointestinal intolerance, AUGMENTIN should be taken at the start of a meal.

HOW SUPPLIED

AUGMENTIN 250-mg Tablets

Each white oval filmcoated tablet, debossed with AUGMENTIN on 1 side and 250/125 on the other side, contains 250 mg amoxicillin as the trihydrate and 125 mg clavulanic acid as the potassium salt.

Bottles of 30 | NDC 54868-0387-1

Store tablets at or below 25°C (77°F). Dispense in original container.

CLINICAL STUDIES

Data from 2 pivotal studies in 1,191 patients treated for either lower respiratory tract infections or complicated urinary tract infections compared a regimen of 875-mg tablets of AUGMENTIN every 12 hours to 500-mg tablets of AUGMENTIN dosed every 8 hours (584 and 607 patients, respectively). Comparable efficacy was demonstrated between the every 12 hours and every 8 hours dosing regimens. There was no significant difference in the percentage of adverse events in each group. The most frequently reported adverse event was diarrhea; incidence rates were similar for the 875-mg every 12 hours and 500-mg every 8 hours dosing regimens (14.9% and 14.3%, respectively); however, there was a statistically significant difference (P < 0.05) in rates of severe diarrhea or withdrawals with diarrhea between the regimens: 1.0% for 875-mg every 12 hours dosing versus 2.5% for the 500-mg every 8 hours dosing.

In 1 of these pivotal studies, 629 patients with either pyelonephritis or a complicated urinary tract infection (i.e., patients with abnormalities of the urinary tract that predispose to relapse of bacteriuria following eradication) were randomized to receive either 875-mg tablets of AUGMENTIN every 12 hours or 500-mg tablets of AUGMENTIN every 8 hours in the following distribution:

 | 875 mg q12h | 500 mg q8h
Pyelonephritis | 173 patients | 188 patients
Complicated UTI | 135 patients | 133 patients
Total patients | 308 | 321

The number of bacteriologically evaluable patients was comparable between the 2 dosing regimens. AUGMENTIN produced comparable bacteriological success rates in patients assessed 2 to 4 days immediately following end of therapy. The bacteriologic efficacy rates were comparable at 1 of the follow-up visits (5 to 9 days post-therapy) and at a late post-therapy visit (in the majority of cases, this was 2 to 4 weeks post-therapy), as seen in the table below:

 | 875 mg q12h | 500 mg q8h
2 to 4 days | 81%, n = 58 | 80%, n = 54
5 to 9 days | 58.5%, n = 41 | 51.9%, n = 52
2 to 4 weeks | 52.5%, n = 101 | 54.8%, n = 104

As noted before, though there was no significant difference in the percentage of adverse events in each group, there was a statistically significant difference in rates of severe diarrhea or withdrawals with diarrhea between the regimens.

REFERENCES

1. National Committee for Clinical Laboratory Standards. Methods for Dilution Antimicrobial Susceptibility Tests for Bacteria that Grow Aerobically - Third Edition. Approved Standard NCCLS Document M7-A3, Vol. 13, No. 25. NCCLS, Villanova, PA, December 1993.
2. National Committee for Clinical Laboratory Standards. Performance Standards for Antimicrobial Disk Susceptibility Tests - Fifth Edition. Approved Standard NCCLS Document M2-A5, Vol. 13, No. 24. NCCLS, Villanova, PA, December 1993.
3. Swanson-Biearman B, Dean BS, Lopez G, Krenzelok EP. The effects of penicillin and cephalosporin ingestions in children less than six years of age. Vet Hum Toxicol. 1988;30:66-67.

AUGMENTIN is a registered trademark of GlaxoSmithKline.

CLINITEST is a registered trademark of Miles, Inc.

CLINISTIX is a registered trademark of Bayer Corporation.

GlaxoSmithKline

Research Triangle Park, NC 27709

©2009, GlaxoSmithKline. All rights reserved.

September 2009 AUT:17PI

Relabeling and Repackaging by:
Physicians Total Care, Inc.
Tulsa, OK 74146

PRINCIPAL DISPLAY PANEL

Augmentin

250 mg

500 mg

875 mg